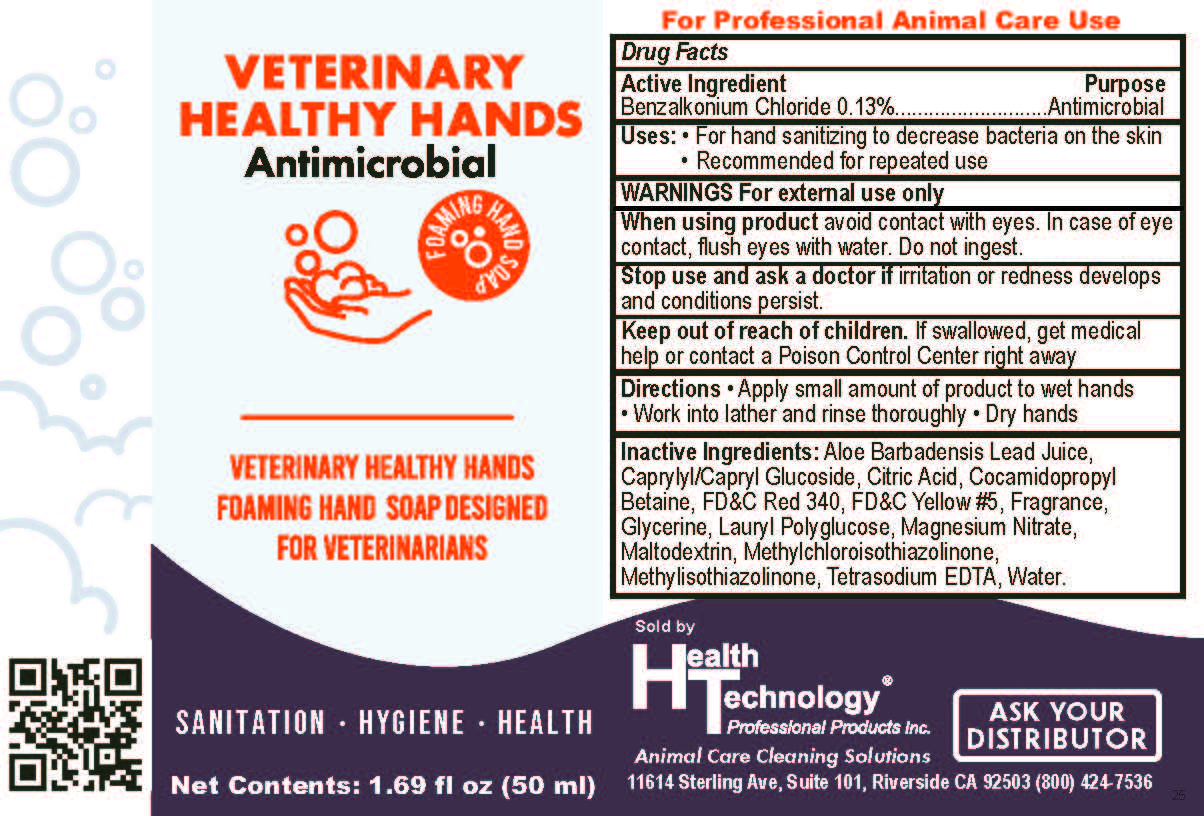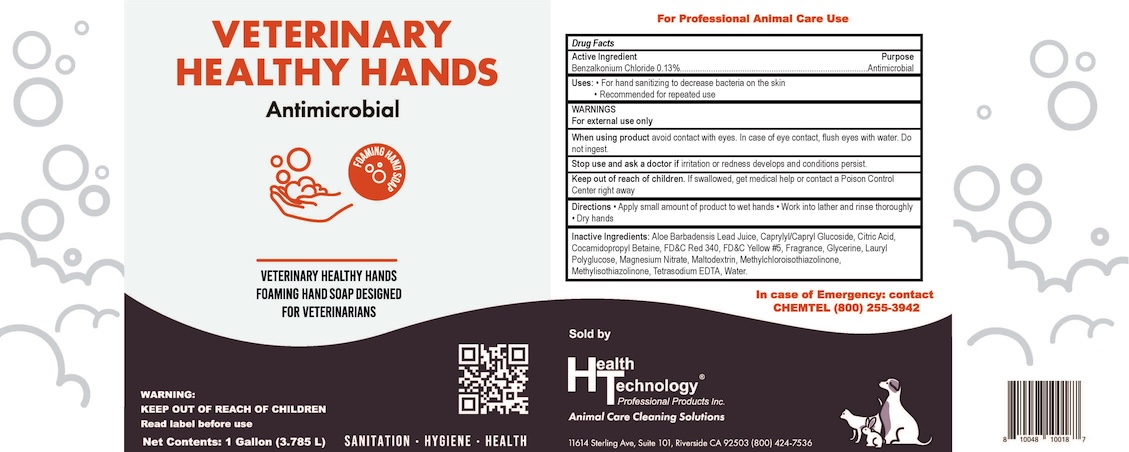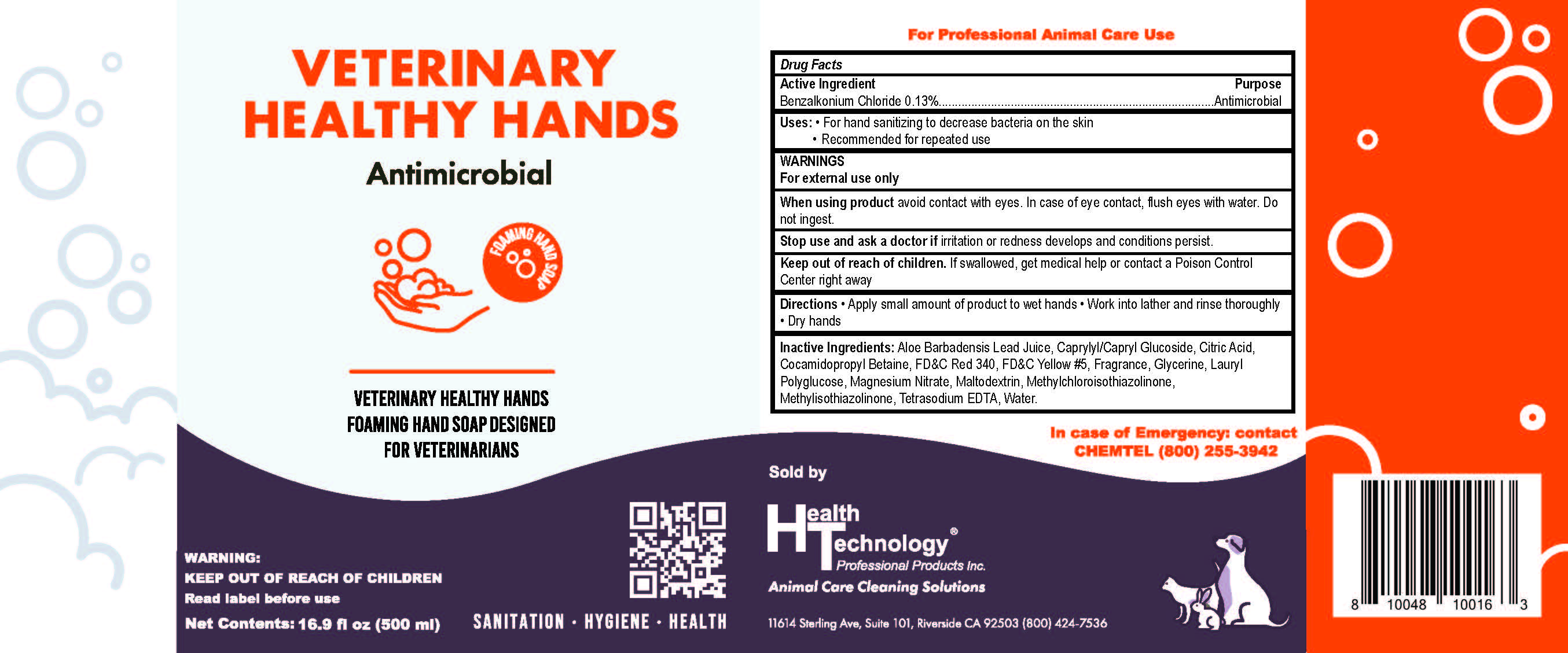 DRUG LABEL: Antimicrobial Foaming Hand
NDC: 81775-100 | Form: SOAP
Manufacturer: Health Technology Professional Products, Inc
Category: otc | Type: HUMAN OTC DRUG LABEL
Date: 20250307

ACTIVE INGREDIENTS: BENZALKONIUM CHLORIDE 0.0013 g/1 mL
INACTIVE INGREDIENTS: MAGNESIUM NITRATE; GLYCERIN; EDETATE SODIUM; FD&C RED NO. 40; COCAMIDOPROPYL BETAINE; CITRIC ACID MONOHYDRATE; FD&C YELLOW NO. 5; ALOE VERA LEAF; WATER; CAPRYLYL GLUCOSIDE; METHYLCHLOROISOTHIAZOLINONE; METHYLISOTHIAZOLINONE; MALTODEXTRIN; LAURYL GLUCOSIDE

Health Technology - Antimicrobial Foaming Hand Soap

Active Ingredient (in each use)

Benzalkonium Chloride .13%

Purpose

Antimicrobial

Uses

• For hand sanitizing to decrease bacteria on the skin

• Recommended for repeated use

Warnings

For external use only

When using this product

Avoid contact with eyes. In case of contact flush eyes with water. Do not ingest,

Stop use and ask a doctor if

irritation or redness develop and condition persists.

Keep Out Of Reach Of Children

If swallowed get medical help or contact a Poison Control Center immediately.

Directions

- Apply small amount of product to wet hands • Work into lather and rinse thoroughly • Dry hands

Inactive ingredinets

Aloe Barbadensis Lead Juice, Caprylyl/Capryl Glucoside, Citric Acid, Cocamidopropyl Betaine, FD&C Red 340, FD&C Yellow #5, Fragrance, Glycerine, Lauryl Polyglucose, Magnesium Nitrate, Maltodextrin, Methylchloroisothiazolinone, Methylisothiazolinone, Tetrasodium EDTA, Water

PACKAGE LABEL

Sample

16 oz

1 - Gallon